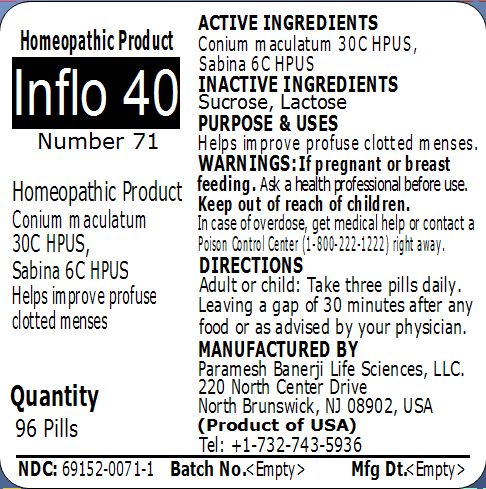 DRUG LABEL: Inflo 40 Number 71
NDC: 69152-0071 | Form: PELLET
Manufacturer: Paramesh Banerji Life Sciences LLC
Category: homeopathic | Type: HUMAN OTC DRUG LABEL
Date: 20150318

ACTIVE INGREDIENTS: CONIUM MACULATUM FLOWERING TOP 30 [hp_C]/1 1; JUNIPERUS SABINA LEAFY TWIG 6 [hp_C]/1 1
INACTIVE INGREDIENTS: SUCROSE; LACTOSE

Active Ingredients

Conium maculatum 30C HPUS, Sabina 6C HPUS

Inactive Ingredients

Sucrose, Lactose

Purpose

Helps improve profuse clotted menses

Uses

Helps improve profuse clotted menses

Warnings

If pregnant or breast feeding ask a health professional before use.

Keep out of reach of children. In case of overdose, get medical help or contact a Poison Control Center (1-800-222-1222) right away.

Direction

Adult or child: Take three pills daily. Leaving a gap of 30 minutes after any food or as advised by your physician.

Manufactured by

Paramesh Banerji Life Sciences, LLC

220 North Center Drive

North Brunswick, NJ 08902, USA

Product of USA

Tel: +1-732-743-5936

Principal Display Panel

Homeopathic Product

Inflo 40

Number 71

Homeopathic Product

Conium maculatum 30C HPUS, Sabina 6C HPUS

Helps improve profuse clotted menses

Quantity

96 Pills